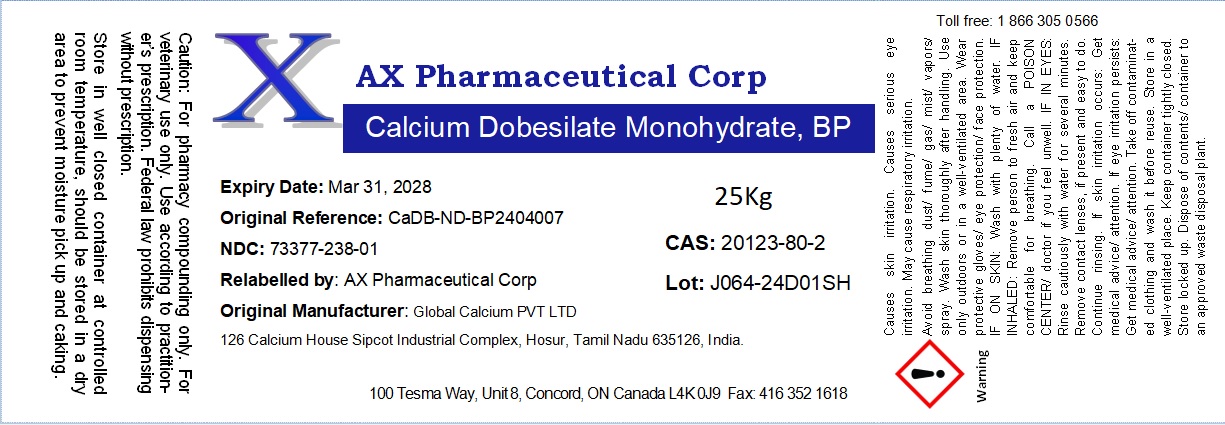 DRUG LABEL: Calcium Dobesilate Monohydrate
NDC: 73377-238 | Form: POWDER
Manufacturer: AX Pharmaceutical Corp.
Category: other | Type: BULK INGREDIENT - ANIMAL DRUG
Date: 20260116

ACTIVE INGREDIENTS: CALCIUM DOBESILATE MONOHYDRATE 1 g/1 g

Calcium Dobesilate Monohydrate